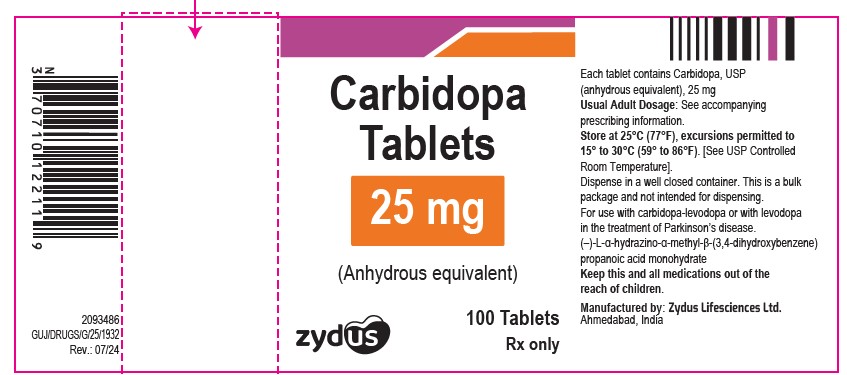 DRUG LABEL: CARBIDOPA
NDC: 70771-1355 | Form: TABLET
Manufacturer: Zydus Lifesciences Limited
Category: prescription | Type: HUMAN PRESCRIPTION DRUG LABEL
Date: 20241126

ACTIVE INGREDIENTS: CARBIDOPA 25 mg/1 1
INACTIVE INGREDIENTS: CELLULOSE, MICROCRYSTALLINE; CROSPOVIDONE; FERRIC OXIDE RED; FERRIC OXIDE YELLOW; HYDROXYPROPYL CELLULOSE, UNSPECIFIED; MAGNESIUM STEARATE; MANNITOL

Carbidopa Tablets

PACKAGE LABEL.PRINCIPAL DISPLAY PANEL

NDC 70771-1355-1

Carbidopa Tablets

Rx only

100 Tablets